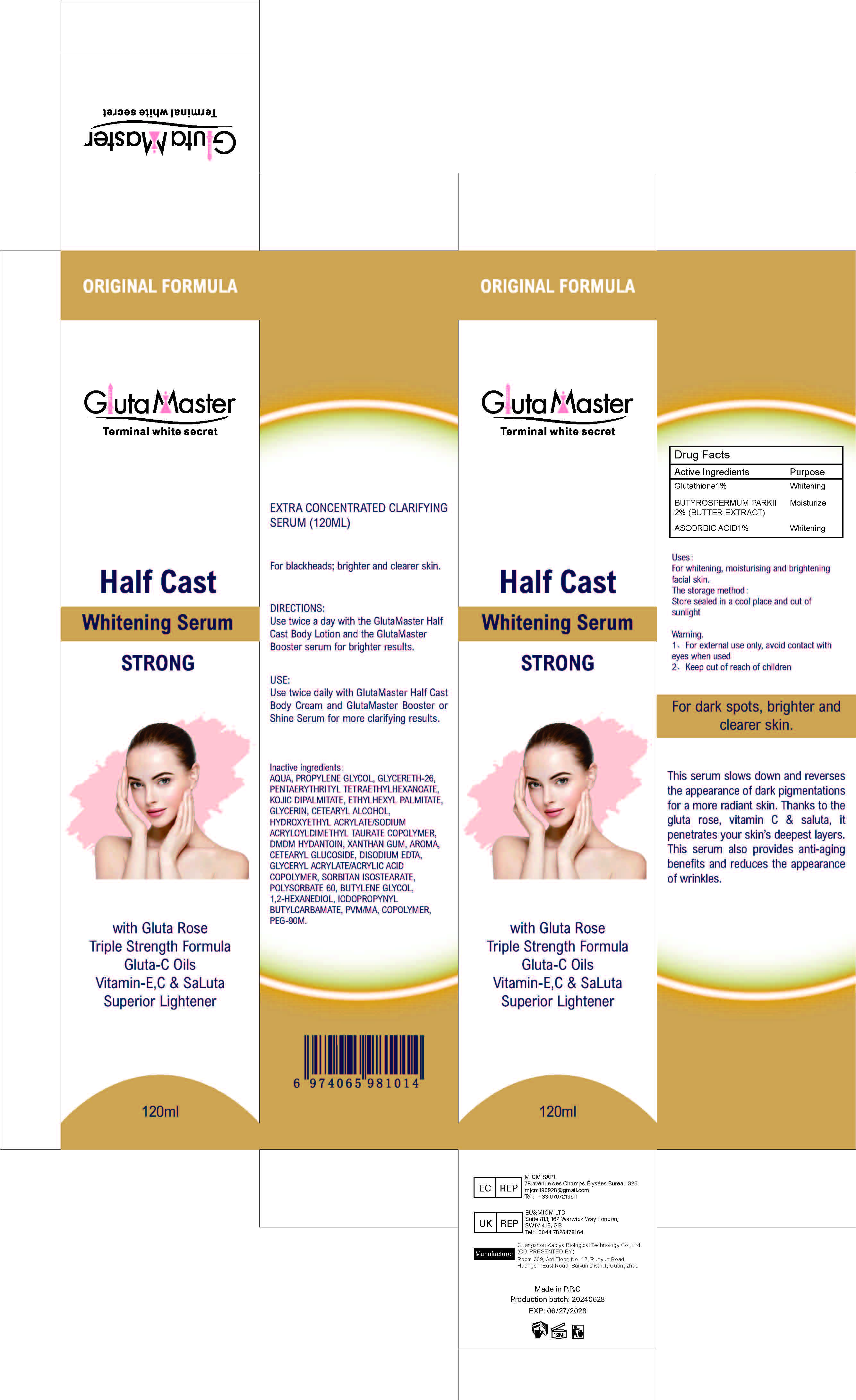 DRUG LABEL: Half Cast Whitening Serum STRONG
NDC: 84423-018 | Form: LIQUID
Manufacturer: Guangzhou Kadiya Biotechnology Co., Ltd.
Category: otc | Type: HUMAN OTC DRUG LABEL
Date: 20240709

ACTIVE INGREDIENTS: BUTYROSPERMUM PARKII (SHEA) BUTTER UNSAPONIFIABLES 2.4 mg/120 mg; GLUTATHIONE 1.2 mg/120 mg; ASCORBIC ACID 1.2 mg/120 mg
INACTIVE INGREDIENTS: POLYETHYLENE GLYCOL 4000000; METHYL VINYL ETHER AND MALEIC ANHYDRIDE COPOLYMER (1100000 WAMW); GLYCERYL ACRYLATE/ACRYLIC ACID COPOLYMER (300000 CP AT 2%); 1,2-HEXANEDIOL; GLYCERETH-26; PENTAERYTHRITYL TETRAETHYLHEXANOATE; EDETATE DISODIUM; HYDROXYETHYL ACRYLATE/SODIUM ACRYLOYLDIMETHYL TAURATE COPOLYMER (45000 MPA.S AT 1%); BUTYLENE GLYCOL; DMDM HYDANTOIN; GLYCERIN; SORBITAN ISOSTEARATE; PROPYLENE GLYCOL; WATER; KOJIC DIPALMITATE; CETOSTEARYL ALCOHOL; XANTHAN GUM; CETEARYL GLUCOSIDE; POLYSORBATE 60; ETHYLHEXYL PALMITATE; IODOPROPYNYL BUTYLCARBAMATE

Uses：
For whitening, moisturising and brightening facial skin.

INACTIVE INGREDIENT

AQUA、PROPYLENE GLYCOL、GLYCERETH-26、PENTAERYTHRITYL TETRAETHYLHEXANOATE、KOJIC DIPALMITATE、ETHYLHEXYL PALMITATE、GLYCERIN、CETEARYL ALCOHOL、HYDROXYETHYL ACRYLATE/SODIUM ACRYLOYLDIMETHYL TAURATE COPOLYMER、DMDM HYDANTOIN、XANTHAN GUM、AROMA、CETEARYL GLUCOSIDE、DISODIUM EDTA、GLYCERYL ACRYLATE/ACRYLIC ACID COPOLYMER、SORBITAN ISOSTEARATE、POLYSORBATE 60、BUTYLENE GLYCOL、1,2-HEXANEDIOL、IODOPROPYNYL BUTYLCARBAMATE、PVM/MA、COPOLYMER、PEG-90M

KEEP OUT OF REACH OF CHILDREN SECTION

INDICATIONS AND USAGE

Use twice a day with the GlutaMaster Half
Cast Body Lotion and the GlutaMaster
Booster serum for brighter results

Active Ingredients
Glutathione1%
（BUTYROSPERMUM PARKII 2%
BUTTER EXTRACT ）
ASCORBIC ACID1%

DOSAGE AND ADMINISTRATION

Use twice daily with GlutaMaster Half Cast
Body Cream and GlutaMaster Booster or
Shine Serum for more clarifying results

Warning.
1、For external use only, avoid contact with eyes when used
2、Keep out of reach of children

PACKAGE LABEL

Active Ingredients
Glutathione1%
（BUTYROSPERMUM PARKII 2%
BUTTER EXTRACT ）
ASCORBIC ACID1%

Uses：
For whitening, moisturising and brightening facial skin.
Indications: For whitening, moisturising and brightening facial skin.
The storage method：
Store sealed in a cool place and out of sunlight

Warning.
1、For external use only, avoid contact with eyes when used
2、Keep out of reach of children

Inactive ingredients：
AQUA、PROPYLENE GLYCOL、GLYCERETH-26、PENTAERYTHRITYL TETRAETHYLHEXANOATE、KOJIC DIPALMITATE、ETHYLHEXYL PALMITATE、GLYCERIN、CETEARYL ALCOHOL、HYDROXYETHYL ACRYLATE/SODIUM ACRYLOYLDIMETHYL TAURATE COPOLYMER、DMDM HYDANTOIN、XANTHAN GUM、AROMA、CETEARYL GLUCOSIDE、DISODIUM EDTA、GLYCERYL ACRYLATE/ACRYLIC ACID COPOLYMER、SORBITAN ISOSTEARATE、POLYSORBATE 60、BUTYLENE GLYCOL、1,2-HEXANEDIOL、IODOPROPYNYL BUTYLCARBAMATE、PVM/MA、COPOLYMER、PEG-90M